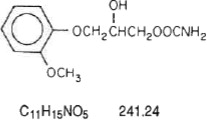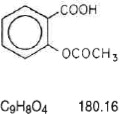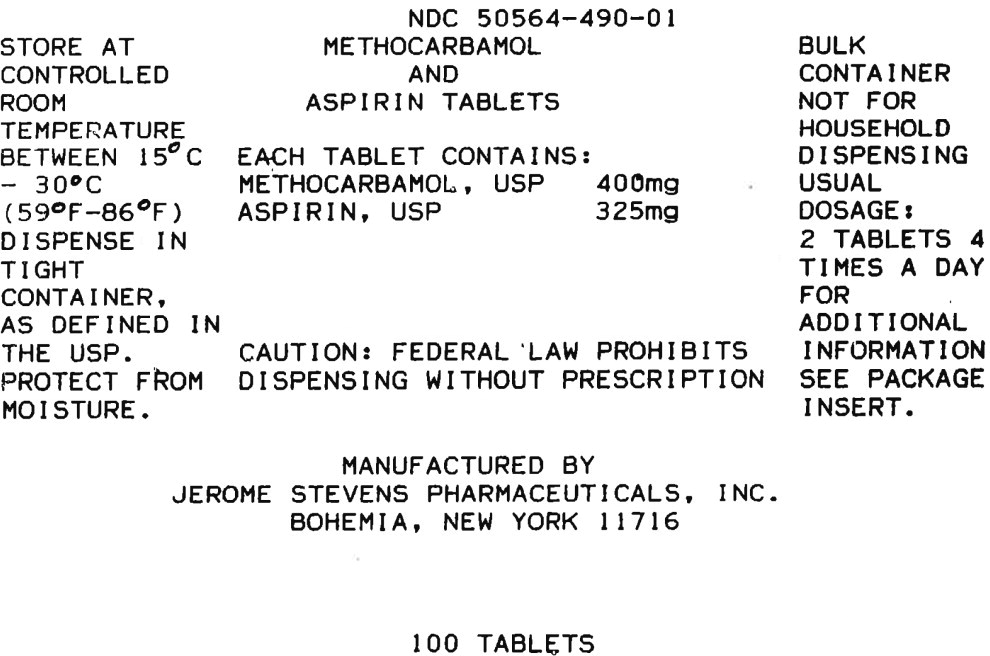 DRUG LABEL: Methocarbamol and Aspirin
NDC: 50564-490 | Form: TABLET
Manufacturer: Jerome Stevens Pharmaceuticals, Inc.
Category: prescription | Type: HUMAN PRESCRIPTION DRUG LABEL
Date: 20240716

ACTIVE INGREDIENTS: methocarbamol 400 mg/1 1; aspirin 325 mg/1 1
INACTIVE INGREDIENTS: STARCH, CORN; povidone; croscarmellose sodium; magnesium stearate; microcrystalline cellulose; SODIUM STARCH GLYCOLATE TYPE A; silicon dioxide; stearic acid

Methocarbamol and Aspirin Tablets

Rx only

Jerome Stevens Pharmaceuticals, Inc.

DESCRIPTION

Each tablet, for oral administration contains:

Methocarbamol, USP 400 mg

Aspirin, USP 325 mg

Inactive Ingredients: Pregelatinized starch, povidone, croscarmellose sodium, magnesium stearate, microcrystalline cellulose, sodium starch glycolate, colloidal silicon dioxide, stearic acid.

The chemical name of methocarbamol is 3-(2-meth-oxyphenoxy)-1,2-propanediol 1-carbamate and has the chemical formula C11H15NO5. Its molecular weight is 241.24. Methocarbamol is a white powder, sparingly soluble in water and chloroform, soluble in alcohol (only with heating) and propylene glycol, and insoluble in benzene and n-hexane. The structural formula is shown below.

The aspirin component is 2-(acetyloxy)-, Benzoic acid, a white crystal, commonly tabular or needle-like, or white, crystalline powder. Is odorless or has a faint odor. Is stable in dry air; in moist air it gradually hydrolyzes to salicylic and acetic acids. Slightly soluble in water; freely soluble in alcohol; soluble in chloroform and in ether; sparingly soluble in absolute ether and is represented by the following structural formula:

CLINICAL PHARMACOLOGY

Methocarbamol and Aspirin provides a double approach to the management of discomforts associated with musculoskeletal disorders.

Methocarbamol

The mechanism of action of methocarbamol in humans has not been established, but may be due to general central nervous system depression. It has no direct action on the contractile mechanism of striated muscle, the motor end plate or the nerve fiber.

Aspirin

Aspirin (acetylsalicylic acid) works by inhibiting the body's production of prostaglandins, including prostaglandins involved in inflammation. Prostaglandins cause pain sensations by stimulating muscle contractions and dilating blood vessels throughout the body. In the CNS, aspirin works on the hypothalamus heat-regulating center to reduce fever, however, other mechanisms may be involved.

PHARMACOKINETICS

In healthy volunteers, the plasma clearance of methocarbamol ranges between 0.20 and 0.80 L/h/kg, the mean plasma elimination half-life ranges between 1 and 2 hours, and the plasma protein binding ranges between 46% and 50%.

Methocarbamol is metabolized via dealkylation and hydroxylation. Conjugation of methocarbamol also is likely. Essentially all methocarbamol metabolites are eliminated in the urine. Small amounts of unchanged methocarbamol also are excreted in the urine.

Aspirin is hydrolyzed primarily to salicylic acid in the gut wall and during first-pass metabolism through the liver. Salicylic acid is absorbed rapidly from the stomach, but most of the absorption occurs in the proximal small intestine. Following absorption, salicylate is distributed to most body tissues and fluids, including fetal tissues, breast milk, and the CNS. High concentrations are found in the liver and kidneys. Salicylate is variably bound to serum proteins, particularly albumin.

The biotransformation of aspirin occurs primarily in the liver by the microsomal enzyme system. With a plasma half-life of approximately 15 minutes, aspirin is rapidly hydrolyzed to salicylate. At low doses, salicylate elimination follows first-order kinetics. The plasma half-life of salicylate is approximately 2 to 3 hours.

Approximately 10% of aspirin is excreted as unchanged salicylate in the urine. The major metabolites excreted in the urine are salicyluric acid (75%), salicyl phenolic glucuronide (10%), salicyl acyl glucuronide (5%), and gentisic and gentisuric acid (less than 1%) each. Eighty to 100% of a single dose is excreted in the urine within 24 to 72 hours.

SPECIAL POPULATIONS

Elderly

The mean (± SD) elimination half-life of methocarbamol in elderly healthy volunteers (mean (± SD) age, 69 (± 4) years) was slightly prolonged compared to a younger (mean (± SD) age, 53.3 (± 8.8) years), healthy population (1.5 (± 0.4) hours versus 1.1 (± 0.27) hours, respectively). The fraction of bound methocarbamol was slightly decreased in the elderly versus younger volunteers (41 to 43% versus 46 to 50%, respectively).

Renally Impaired

The clearance of methocarbamol in 8 renally-impaired patients on maintenance hemodialysis was reduced about 40% compared to 17 normal subjects, although the mean (± SD) elimination half-life in these two groups was similar: 1.2 (± 0.6) versus 1.1 (± 0.3) hours, respectively.

Avoid aspirin in patients with severe renal impairment (glomerular filtration rate less than 10 mL/minute).

Hepatically Impaired

In 8 patients with cirrhosis secondary to alcohol abuse, the mean total clearance of methocarbamol was reduced approximately 70% compared to that obtained in 8 age- and weight-matched normal subjects. The mean (± SD) elimination half-life in the cirrhotic patients and the normal subjects was 3.38 (± 1.62) hours and 1.11 (± 0.27) hours, respectively. The percent of methocarbamol bound to plasma proteins was decreased to approximately 40 to 45% compared to 46 to 50% in the normal subjects.

Avoid aspirin in patients with severe hepatic impairment.

INDICATIONS AND USAGE

Methocarbamol and Aspirin tablets are indicated as an adjunct to rest, physical therapy and other measures for the relief of discomfort associated with acute, painful musculoskeletal conditions. The mode of action of methocarbamol has not been clearly identified but may be related to its sedative properties. Methocarbamol does not directly relax tense skeletal muscles in man.

CONTRAINDICATIONS

Hypersensitivity to methocarbamol or aspirin.

WARNINGS

Methocarbamol

Since methocarbamol may possess a general central nervous system depressant effect, patients receiving methocarbamol should be cautioned about combined effects with alcohol and other CNS depressants.

Fetal Toxicity

Premature Closure of Fetal Ductus Arteriosus:

Avoid use of NSAIDs, including Methocarbamol and Aspirin Tablets , in pregnant women at about 30 weeks gestation and later. NSAIDs including Methocarbamol and Aspirin Tablets, increase the risk of premature closure of the fetal ductus arteriosus at approximately this gestational age.

Oligohydramnios/Neonatal Renal Impairment:

Use of NSAIDs, including Methocarbamol and Aspirin Tablets, at about 20 weeks gestation or later in pregnancy may cause fetal renal dysfunction leading to oligohydramnios and, in some cases, neonatal renal impairment. These adverse outcomes are seen, on average, after days to weeks of treatment, although oligohydramnios has been infrequently reported as soon as 48 hours after NSAID initiation.

Oligohydramnios is often, but not always, reversible with treatment discontinuation. Complications of prolonged oligohydramnios may, for example, include limb contractures and delayed lung maturation. In some post marketing cases of impaired neonatal renal function, invasive procedures such as exchange transfusion or dialysis were required.

If NSAID treatment is necessary between about 20 weeks and 30 weeks gestation, limit Methocarbamol and Aspirin Tablets use to the lowest effective dose and shortest duration possible. Consider ultrasound monitoring of amniotic fluid if Methocarbamol and Aspirin Tablets treatment extends beyond 48 hours. Discontinue Methocarbamol and Aspirin Tablets if oligohydramnios occurs and follow up according to clinical practice (see PRECAUTIONS; Pregnancy).

Use In Activities Requiring Mental Alertness

Methocarbamol may impair mental and/or physical abilities required for performance of hazardous tasks, such as operating machinery or driving a motor vehicle. Patients should be cautioned about operating machinery, including automobiles, until they are reasonably certain that methocarbamol therapy does not adversely affect their ability to engage in such activities.

Serious Skin Reactions

NSAIDs, including aspirin, a component of Methocarbamol and Aspirin Tablets, can cause serious skin adverse reactions such as exfoliative dermatitis, Stevens-Johnson Syndrome (SJS), and toxic epidermal necrolysis (TEN), which can be fatal. NSAIDs can also cause fixed drug eruption (FDE). FDE may present as a more severe variant known as generalized bullous fixed drug eruption (GBFDE), which can be life-threatening. These serious events may occur without warning. Inform patients about the signs and symptoms of serious skin reactions, and to discontinue the use of Methocarbamol and Aspirin Tablets at the first appearance of skin rash or any other sign of hypersensitivity. Methocarbamol and Aspirin Tablets is contraindicated in patients with previous serious skin reactions to NSAIDs [see CONTRAINDICATIONS].

Drug Reaction with Eosinophilia and Systemic Symptoms (DRESS) has been reported in patients taking NSAIDs such as Methocarbamol and Aspirin Tablets. Some of these events have been fatal or life-threatening. DRESS typically, although not exclusively presents with fever, rash, lymphadenopathy and/or facial swelling. Other clinical manifestations may include hepatitis, nephritis, hematological abnormalities, myocarditis, or myositis. Sometimes symptoms of DRESS may resemble an acute viral infection. Eosinophilia is often present. Because this disorder is variable in its presentation, other organ systems not noted here may be involved. It is important to note that early manifestations of hypersensitivity, such as fever or lymphadenopathy, may be present even though rash is not evident. If such signs or symptoms are present, discontinue Methocarbamol and Aspirin Tablets and evaluate the patient immediately.

PRECAUTIONS

General

Products containing aspirin should be administered with caution to patients with gastritis or peptic ulceration, or those receiving hypoprothrombinemic anticoagulants.

Aspirin has been associated with elevated hepatic enzymes, blood urea nitrogen and serum creatinine, hyperkalemia, proteinuria, and prolonged bleeding time.

Hemorrhage

Aspirin may increase the likelihood of hemorrhage due to its effect on the gastric mucosa and platelet function (prolongation of bleeding time). Salicylates should be used with caution in the presence of peptic ulcer or coagulation abnormalities.

Information for Patients

Methocarbamol may cause drowsiness or dizziness, which may impair their ability to operate motor vehicles or machinery.

Because methocarbamol may possess a general CNS-depressant effect, patients should be cautioned about combined effects with alcohol and other CNS depressants.

Fetal Toxicity

Inform pregnant women to avoid use of aspirin and other NSAIDs starting at 30 weeks gestation because of the risk of the premature closing of the fetal ductus arteriosus. If treatment with Methocarbamol and Aspirin Tablets is needed for a pregnant woman between about 20 to 30 weeks gestation, advise her that she may need to be monitored for oligohydramnios, if treatment continues for longer than 48 hours (see WARNINGS, Fetal Toxicity, PRECAUTIONS; Pregnancy).

Serious Skin Reactions, including DRESS

Advise patients to stop taking Methocarbamol and Aspirin Tablets immediately if they develop any type of rash or fever and to contact their healthcare provider as soon as possible (see WARNINGS).

Drug Interactions

See WARNINGS and PRECAUTIONS for interaction with CNS drugs and alcohol.

Methocarbamol may inhibit the effect of pyridostigmine bromide. Therefore, methocarbamol should be used with caution in patients with myasthenia gravis receiving anticholinesterase agents.

Angiotensin Converting Enzyme (ACE) Inhibitors: The hyponatremic and hypotensive effects of ACE inhibitors may be diminished by the concomitant administration of aspirin due to its indirect effect on the renin-angiotensin conversion pathway.

Acetazolamide: Concurrent use of aspirin and acetazolamide can lead to high serum concentrations of acetazolamide (and toxicity) due to competition at the renal tubule for secretion.

Anticoagulant Therapy (Heparin and Warfarin): Patients on anticoagulation therapy are at increased risk for bleeding because of drug-drug interactions and the effect on platelets. Aspirin can displace warfarin from protein binding sites, leading to prolongation of both the prothrombin time and the bleeding time. Aspirin can increase the anticoagulant activity of heparin, increasing bleeding risk.

Anticonvulsants: Salicylate can displace protein-bound phenytoin and valproic acid, leading to a decrease in the total concentration of phenytoin and an increase in serum valproic acid levels.

Beta Blockers: The hypotensive effects of beta blockers may be diminished by the concomitant administration of aspirin due to inhibition of renal prostaglandins, leading to decreased renal blood flow, and salt and fluid retention.

Diuretics: The effectiveness of diuretics in patients with underlying renal or cardiovascular disease may be diminished by the concomitant administration of aspirin due to inhibition of renal prostaglandins, leading to decreased renal blood flow and salt and fluid retention.

Methotrexate: Aspirin may enhance the serious side and toxicity of methotrexate due to displacement from its plasma protein binding sites and/or reduced renal clearance.

Nonsteroidal Anti-inflammatory Drugs (NSAID's): The concurrent use of aspirin with other NSAID's should be avoided because this may increase bleeding or lead to decreased renal function. Aspirin may enhance the serious side effects and toxicity of ketorolac, due to displacement from its plasma protein binding sites and/or reduced renal clearance.

Oral Hypoglycemics Agents: Aspirin may increase the serum glucose-lowering action of insulin and sulfonylureas leading to hypoglycemia.

Uricosuric Agents: Salicylates antagonize the uricosuric action of probenecid or sulfinpyrazone.

Drug/Laboratory Test Interactions

Methocarbamol may cause a color interference in certain screening tests for 5-hydroxyindoleacetic acid (5-HIAA) using nitrosonaphthol reagent and in screening tests for urinary vanillylmandelic acid (VMA) using the Gitlow method.

Salicylates may increase the protein bound iodine (PBI) result by competing for the protein binding sites on pre-albumin and possibly thyroid-binding globulins.

Carcinogenesis, mutagenesis, impairment of fertility

Long-term studies to evaluate the carcinogenic potential of methocarbamol have not been performed. No studies have been conducted to assess the effect of methocarbamol on mutagenesis or its potential to impair fertility.

Long-term studies in animals to evaluate the carcinogenic potential of aspirin have not been conducted. Aspirin induced chromosome aberrations in cultured human fibroblasts. Aspirin has been shown to inhibit ovulation in rats.

Pregnancy

Teratogenic effects – Pregnancy Category C

Animal reproduction studies have not been conducted with methocarbamol. It is also not known whether methocarbamol can cause fetal harm when administered to a pregnant woman or can affect reproduction capacity. Methocarbamol should be given to a pregnant woman only if clearly needed.

Safe use of Methocarbamol has not been established with regard to possible adverse effects upon fetal development. There have been reports of fetal and congenital abnormalities following in utero exposure to methocarbamol. Therefore, Methocarbamol should not be used in women who are or may become pregnant and particularly during early pregnancy unless in the judgment of the physician the potential benefits outweigh the possible hazards (see WARNINGS).

Nonteratogenic Effects

Risk Summary

Use of NSAIDs, including aspirin, can cause premature closure of the fetal ductus arteriosus and fetal renal dysfunction leading to oligohydramnios and, in some cases, neonatal renal impairment. Because of these risks, limit dose and duration of Methocarbamol and Aspirin Tablets use between 20 and 30 weeks of gestation, and avoid Methocarbamol and Aspirin Tablets use at about 30 weeks of gestation and later in pregnancy [see WARNINGS, Fetal Toxicity].

Premature Closure of Fetal Ductus Arteriosus

Use of NSAIDs, including aspirin, at about 30 weeks gestation or later in pregnancy increases the risk of premature closure of the fetal ductus arteriosus.

Oligohydramnios/Neonatal Renal Impairment

Use of NSAIDs at about 20 weeks gestation or later in pregnancy has been associated with cases of fetal renal dysfunction leading to oligohydramnios, and in some cases, neonatal renal impairment.

Data from observational studies regarding other potential embryofetal risks of NSAID use in women in the first or second trimesters of pregnancy are inconclusive.

Based on animal data, prostaglandins have been shown to have an important role in endometrial vascular permeability, blastocyst implantation, and decidualization. In animal studies, administration of prostaglandin synthesis inhibitors such as aspirin, resulted in increased pre- and post-implantation loss. Prostaglandins also have been shown to have an important role in fetal kidney development. In published animal studies, prostaglandin synthesis inhibitors have been reported to impair kidney development when administered at clinically relevant doses.

The estimated background risk of major birth defects and miscarriage for the indicated population(s) is unknown. All pregnancies have a background risk of birth defect, loss, or other adverse outcomes. In the U.S. general population, the estimated background risk of major birth defects and miscarriage in clinically recognized pregnancies is 2-4% and 15-20%, respectively.

Clinical Considerations

Fetal/Neonatal/ Adverse Reactions

Premature Closure of Fetal Ductus Arteriosus:

Avoid use of NSAIDs in women at about 30 weeks gestation and later in pregnancy, because NSAIDs, including Methocarbamol and Aspirin Tablets, can cause premature closure of the fetal ductus arteriosus (see WARNINGS, Fetal Toxicity).

Oligohydramnios/Neonatal Renal Impairment

If an NSAID is necessary at about 20 weeks gestation or later in pregnancy, limit the use to the lowest effective dose and shortest duration possible. If Methocarbamol and Aspirin Tablets treatment extends beyond 48 hours, consider monitoring with ultrasound for oligohydramnios. If oligohydramnios occurs, discontinue Methocarbamol and Aspirin Tablets and follow up according to clinical practice (see WARNINGS, Fetal Toxicity).

Data

Human Data

Premature Closure of Fetal Ductus Arteriosus:

Published literature reports that the use of NSAIDs at about 30 weeks of gestation and later in pregnancy may cause premature closure of the fetal ductus arteriosus.

Oligohydramnios/Neonatal/ Renal Impairment:

Published studies and post marketing reports describe maternal NSAID use at about 20 weeks gestation or later in pregnancy associated with fetal renal dysfunction leading to oligohydramnios, and in some cases, neonatal renal impairment. These adverse outcomes are seen, on average, after days to weeks of treatment, although oligohydramnios has been infrequently reported as soon as 48 hours after NSAID initiation. In many cases, but not all, the decrease in amniotic fluid was transient and reversible with cessation of the drug. There have been a limited number of case reports of maternal NSAID use and neonatal renal dysfunction without oligohydramnios, some of which were irreversible. Some cases of neonatal renal dysfunction required treatment with invasive procedures, such as exchange transfusion or dialysis.

Methodological limitations of these post marketing studies and reports include lack of a control group; limited information regarding dose, duration, and timing of drug exposure; and concomitant use of other medications. These limitations preclude establishing a reliable estimate of the risk of adverse fetal and neonatal outcomes with maternal NSAID use. Because the published safety data on neonatal outcomes involved mostly preterm infants, the generalizability of certain reported risks to the full-term infant exposed to NSAIDs through maternal use is uncertain.

Labor or Delivery

Salicylates readily cross the placenta and by inhibiting prostaglandin synthesis, may cause constriction of ductus arteriosus resulting in pulmonary hypertension and increased fetal mortality and, possibly other untoward fetal effects. Aspirin use in pregnancy can also result in alteration in maternal and neonatal hemostasis mechanisms. Maternal aspirin use during later stages of pregnancy may cause low birth weight, increased incidence of intracranial hemorrhage in premature infants, stillbirths and neonatal death. Use during pregnancy, especially in the third trimester, should be avoided.

Nursing Mothers

Methocarbamol and/or its metabolites are excreted in the milk of dogs; however, it is not known whether methocarbamol or its metabolites are excreted in human milk.

Salicylic acid has been detected in breast milk. Adverse effects on platelet function in the nursing infant exposed to aspiring in breast milk may be a potential risk. Furthermore, the risk of Reye Syndrome cause by salicylate in breast milk is unknown.

Because many drugs are excreted in human milk, caution should be exercised when Methocarbamol and Aspirin Tablets are administered to a nursing woman.

Pediatric use

Safety and effectiveness of Methocarbamol and Aspirin Tablets in pediatric patients below the age of 12 have not been established.

ADVERSE REACTIONS

Adverse reactions reported coincident with the administration of methocarbamol include:

Body as a whole

Anaphylactic reaction, angioneurotic edema, fever, headache

Cardiovascular system

Bradycardia, flushing, hypotension, syncope, thrombophlebitis

Digestive system

Dyspepsia, jaundice (including cholestatic jaundice), nausea and vomiting

Hemic and lymphatic system

Leukopenia

Immune system

Hypersensitivity reactions

Nervous system

Amnesia, confusion, diplopia, dizziness or lightheadedness, drowsiness, insomnia, mild muscular

incoordination, nystagmus, sedation, seizures (including grand mal), vertigo

Skin and special senses

Blurred vision, conjunctivitis, nasal congestion, metallic taste, pruritus, rash, urticaria

Aspirin

Aspirin may increase the likelihood of hemorrhage due to its effect on the gastric mucosa and platelet function. Furthermore, aspirin has the potential to cause anaphylaxis in hypersensitive patients as well as angioedema especially in patients with chronic urticaria. Other adverse reactions due to aspirin use include anorexia, reversible hepatotoxicity, leukopenia, thrombocytopenia, purpura, decreased plasma iron concentration, and shortened erythrocyte survival time.

Adverse reactions that have been associated with the use of aspirin include: nausea and other gastrointestinal discomfort, gastritis, gastric erosion, vomiting, constipation, diarrhea, angio-edema, asthma, rash, pruritis, urticaria, exfoliative dermatitis, Stevens-Johnson Syndrome

(SJS), toxic epidermal necrolysis (TEN), and fixed drug eruption (FDE) (see WARNINGS). Gastrointestinal discomfort may be minimized by taking Methocarbamol and Aspirin with food.

To report SUSPECTED ADVERSE REACTIONS, contact Jerome Stevens Pharmaceuticals Inc. at 1-844-686-1019 or FDA at 1-800-FDA-1088 or www.fda.gov/medwatch.

OVERDOSAGE

Limited information is available on the acute toxicity of methocarbamol. Overdose of methocarbamol is frequently in conjunction with alcohol or other CNS depressants and includes the following symptoms: nausea, drowsiness, blurred vision, hypotension, seizures, and coma.

In post-marketing experience, deaths have been reported with an overdose of methocarbamol alone or in the presence of other CNS depressants, alcohol or psychotropic drugs.

Early signs of acute aspirin (salicylate) overdose including tinnitus occur at plasma concentrations approaching 200 mcg/mL. Plasma concentrations of aspirin above 300 mcg/mL are toxic. Severe toxic effects are associated with levels above 400 mcg/mL. A single lethal dose of aspirin in adults is not known with certainty but death may be expected at 30 g. For real or suspected overdose, a Poison Control Center should be contacted immediately.

In acute salicylate overdose, severe acid-base and electrolyte disturbances may occur and are complicated by hyperthermia and dehydration, and coma. Respiratory alkalosis occurs early while hyperventilation is present, but is quickly followed by metabolic acidosis. Serious symptoms such as depression, coma, and respiratory failure progress rapidly.

Salicylism (chronic salicylate toxicity) may be noted by symptoms such as dizziness, tinnitus, difficulty hearing, nausea, vomiting, diarrhea, and mental confusion. More severe salicylism may result in respiratory alkalosis.

Treatment of Overdosage: Supportive therapy for 24 hours, as methocarbamol is excreted within that time. If salicylate intoxication occurs, especially in children, the hyperpnea may be controlled with sodium bicarbonate. Judicious use of 5% CO2 with 95% O2 may be of benefit. Abnormal electrolyte patterns should be corrected with appropriate fluid therapy.

DOSAGE AND ADMINISTRATION

Adults and children over 12 years of age: Two tablets four times daily. Three tablets four times daily may be used in severe conditions for one to three days in patient who are able to tolerate salicylates. These dosage recommendations provide respectively 3.2 and 4.8 grams of methocarbamol per day.

HOW SUPPLIED

Methocarbamol and Aspirin supplied as pink and white laminated, compressed tablets monogrammed JSP 490 in bottles of 100 (NDC 50564-490-01), 500 (NDC 50564-490-05).

Store at controlled room temperature 15° - 30°C (59° - 86°F). Protect from moisture.

Dispense in a tight container, as defined in the USP.

CAUTION: Federal law prohibits dispensing without prescription.

Manufactured by:
Jerome Stevens Pharmaceuticals, Inc.
Bohemia, New York 11716

REV. 07/24 MG #6317

Principal Display Panel - 100 Tablet Bottle Label

NDC 50564-490-01

METHOCARBAMOL
AND
ASPIRIN TABLETS

EACH TABLET CONTAINS:
METHOCARBAMOL, USP 400mg

ASPIRIN, USP 325mg

CAUTION: FEDERAL LAW PROHIBITS
DISPENSING WITHOUT PRESCRIPTION

MANUFACTURED BY
JEROME STEVENS PHARMACEUTICALS, INC

BOHEMIA, NEW YORK 11716

100 TABLETS